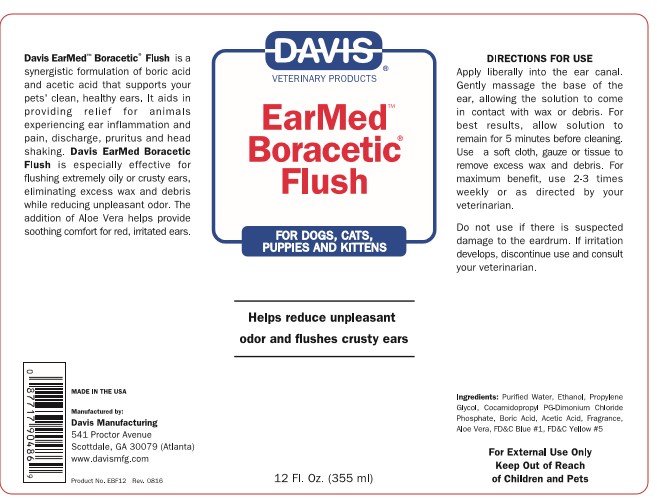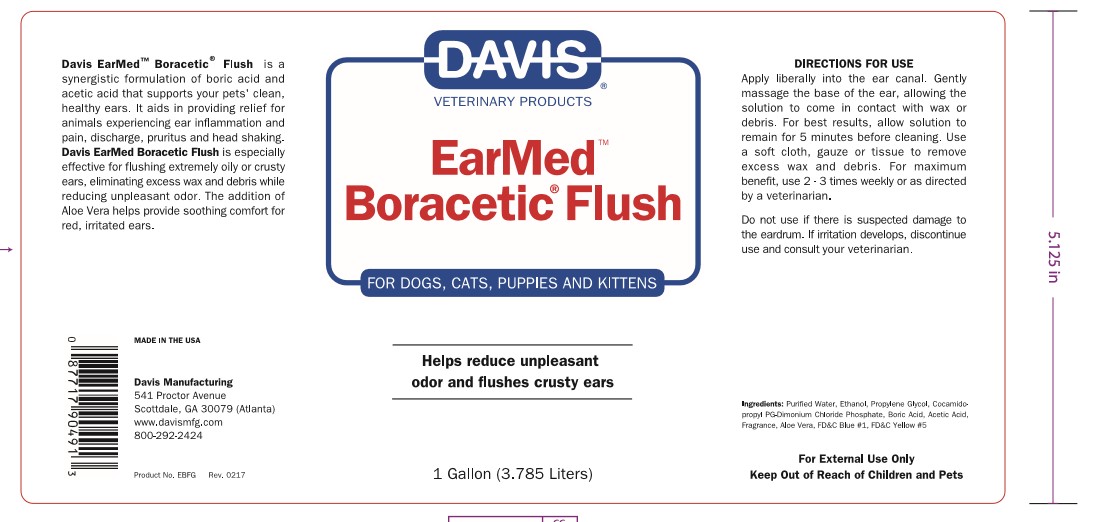 DRUG LABEL: Davis Boracetic
NDC: 62570-150 | Form: RINSE
Manufacturer: Davis Manufacturing and Packaging Inc
Category: animal | Type: OTC ANIMAL DRUG LABEL
Date: 20191018

ACTIVE INGREDIENTS: ACETIC ACID 404.98 mg/1 g; SODIUM BORATE 404.98 mg/1 g
INACTIVE INGREDIENTS: WATER; ALCOHOL; PROPYLENE GLYCOL; COCAMIDOPROPYL PROPYLENE GLYCOL-DIMONIUM CHLORIDE PHOSPHATE; LANOLIN; ALOE VERA LEAF; FD&C BLUE NO. 1; FD&C YELLOW NO. 5

Davis Earmed Boracetic Flush

DESCRIPTION

Davis Earmed Boracetic Flush is a synergistic formula of boric acid and acetic acid that supports your pets' clean, healthy ears.

It aids in providing relief for animals experiencing ear inflammation and pain, discharge, pruritus and head shaking.

Davis Earmed Boracetic Flush is especially effective for flushing exremely oily or crusty ears, eliminating excess wax

and debris while reducing unpleasant odor. The addition of Aloe Vera helps provide soothing comfort for red, irritated ears.

MADE IN THE USA

Manufactured by:

Davis Manufacturing

541 Proctor Avenue

Scottdale, GA 30079 (Atlanta)

www.davismfg.com

INDICATIONS AND USAGE

Directions for use:

Apply liberally into ear canal. Gently massage the base of the ear, allowing the solution to come in

contact with wax or debris. For best results allow solution to remain 5 minuttes before cleaning.

Use a soft cloth, gauze or tissue to remove excess wax and debris. For maximum benefit,

use 2-3 times weekly or as directed by your veterinarian.

INACTIVE INGREDIENT

Ingredients:

Purified water, Ethanol, Propylene Glycol, Cocamidopropyl PG-Dimonium Chloride Phosphate, Boric Acid, Acetic Acid, Fragrance, Aloe Vera, FD&C Blue #1, FD&C Yellow #5

KEEP OUT OF REACH OF CHILDREN

For External Use only

Keep out of reach of children and pets

Do not use if there is suspected damage to the eardrum. If irritation develops, discontinue use and consult a veterinarian.

PACKAGE LABEL

Davis Veterinarian Products

EARMED BORACETIC FLUSH

for dogs, cats, puppies, and kittens

Helps reduce unplesant odor and flushes crusty ears